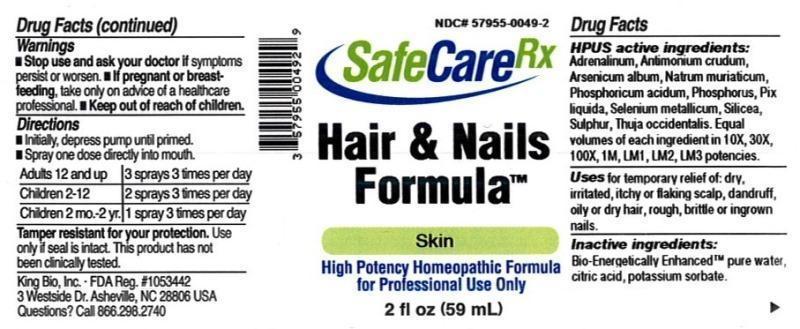 DRUG LABEL: Hair and Nails Formula
NDC: 57955-0049 | Form: LIQUID
Manufacturer: King Bio Inc.
Category: homeopathic | Type: HUMAN OTC DRUG LABEL
Date: 20150311

ACTIVE INGREDIENTS: EPINEPHRINE 10 [hp_X]/59 mL; ANTIMONY TRISULFIDE 10 [hp_X]/59 mL; ARSENIC TRIOXIDE 10 [hp_X]/59 mL; SODIUM CHLORIDE 10 [hp_X]/59 mL; PHOSPHORIC ACID 10 [hp_X]/59 mL; PHOSPHORUS 10 [hp_X]/59 mL; PINE TAR 10 [hp_X]/59 mL; SELENIUM 10 [hp_X]/59 mL; SILICON DIOXIDE 10 [hp_X]/59 mL; SULFUR 10 [hp_X]/59 mL; THUJA OCCIDENTALIS LEAFY TWIG 10 [hp_X]/59 mL
INACTIVE INGREDIENTS: WATER; ANHYDROUS CITRIC ACID; POTASSIUM SORBATE

Hair and Nails Formula™

ACTIVE INGREDIENT

Drug Facts__________________________________________________________________________________________________________

HPUS active ingredients: Adrenalinum, Antimonium crudum, Arsenicum album, Natrum muriaticum, Phosphoricum acidum, Phosphorus, Pix Liquid, Selenium metallicum, Silicea, Sulphur, Thuja occidentalis. Equal volumes of each ingredient in 10X, 30X, 100X, 1M, LM1, LM2, LM3 potencies.

INDICATIONS AND USAGE

Uses for temporary relief of: dry, irritated, itchy or flaking scalp, dandruff, oily or dry hair, rough, brittle or ingrown nails.

Inactive Ingredients:

Bio-Energetically Enhanced™ pure water, citric acid and potassium sorbate.

Warnings

- Stop use and ask your doctor if symptoms persist or worsen.
- If pregnant or breast-feeding, take only on advice of a healthcare professional.

- Keep out of reach of children.

Directions

- Initially, depress pump until primed.
- Spray one dose directly into mouth.
- Adults 12 and up: 3 sprays 3 times per day
- Children 2-12: 2 sprays 3 times per day
- Children 2 mo-2yr: 1 spray 3 times per day

OTHER SAFETY INFORMATION

Tamper resistant for your protection. Use only if safety seal is intact. This product has not been clinically tested.

PURPOSE

Uses for temporary relief of:

- dry, irritated, itchy or flaking scalp
- dandruff
- oily or dry hair
- rough, brittle or ingrown nails